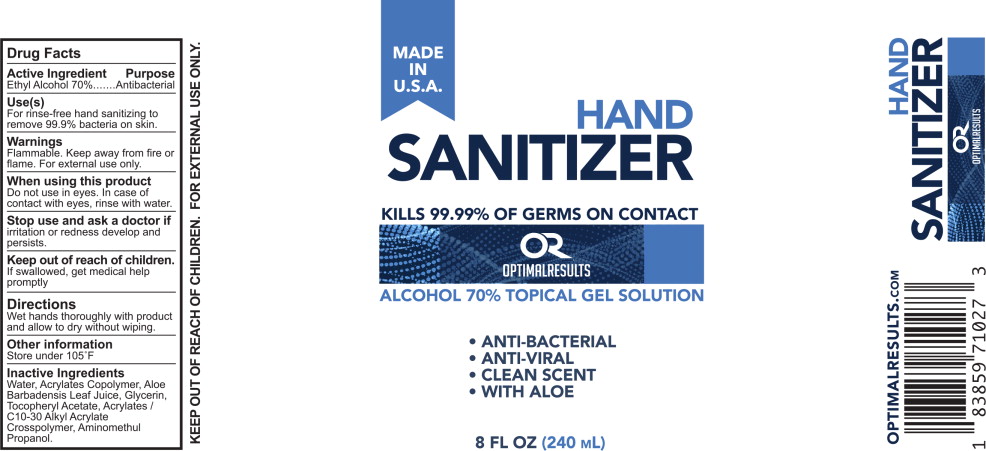 DRUG LABEL: Optimal Results Hand Sanitizer
NDC: 78956-101 | Form: GEL
Manufacturer: HB Media LLC (dba Optimal Results)
Category: otc | Type: HUMAN OTC DRUG LABEL
Date: 20200612

ACTIVE INGREDIENTS: Alcohol 70 mL/100 mL
INACTIVE INGREDIENTS: Water; Butyl Acrylate/Methyl Methacrylate/Methacrylic Acid Copolymer (18000 MW); Aloe Vera Leaf; Glycerin; .Alpha.-Tocopherol Acetate; Carbomer Interpolymer Type A (Allyl Sucrose Crosslinked); Aminomethylpropanol

Drug Facts

Active Ingredients

Ethyl Alcohol 70%.

Purpose

Antibacterial

Use

For rinse-free hand sanitizing to remove 99.9% bacteria on skin.

Warnings

Flammable. Keep away from fire or flame. For external use only.

When using this product

Do not use in eyes. In case of contact with eyes, rinse with water.

Stop use and ask a doctor if

irritation and redness develop and persist.

Keep out of reach of children.

If swallowed, get medical help promptly.

Directions

Wet hands thoroughly with product and allow to dry without wiping.

Other Information

Store under 105°F

Inactive Ingredients

Water, Acrylates Copolymer, Aloe Barbadensis Leaf Juice, Glycerin, Tocopheryl Acetate, Acrylates/ C10-30 Alkyl Acrylate Crosspolymer, Aminomethyl Propanol

Principal Display Panel – Bottle Label

MADE IN U.S.A.

HAND SANITIZER

KILLS 99.9% OF GERMS ON CONTACT

OPTIMAL RESULTS

ALCOHOL 70% TOPICAL GEL SOLUTION

- ANTI-BACTERIAL
- ANTI-VIRAL
- CLEAN SCENT
- WITH ALOE

8 Fl Oz (240 mL)